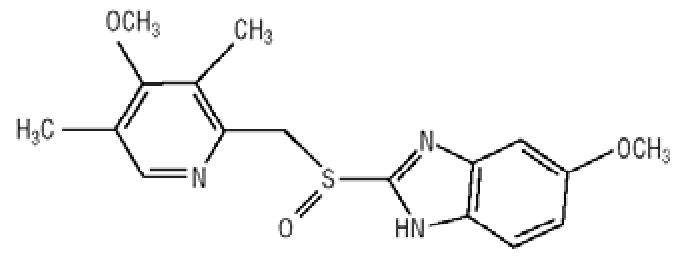 DRUG LABEL: Unknown
Manufacturer: Santarus, Inc.
Category: prescription | Type: HUMAN PRESCRIPTION DRUG LABELING
Date: 20060608

ZEGERID® with Magnesium Hydroxide
(omeprazole/sodium bicarbonate/magnesium hydroxide)

Rx Only

Chewable Tablets

DESCRIPTION

ZEGERID® with Magnesium Hydroxide (omeprazole/sodium bicarbonate/magnesium hydroxide) is a combination of omeprazole, a proton-pump inhibitor, and sodium bicarbonate plus magnesium hydroxide, both of which are antacids. Omeprazole is a substituted benzimidazole, 5-methoxy-2-[[(4-methoxy-3,5-dimethyl-2-pyridinyl)methyl]sulfinyl]-1H-benzimidazole, a racemic mixture of two enantiomers that inhibits gastric acid secretion. Its empirical formula is C17H19N3O3S, with a molecular weight of 345.42. The structural formula is:

Omeprazole is a white to off-white crystalline powder which melts with decomposition at about 155°C. It is a weak base, freely soluble in ethanol and methanol, and slightly soluble in acetone and isopropanol and very slightly soluble in water. The stability of omeprazole is a function of pH; it is rapidly degraded in acid media, but has acceptable stability under alkaline conditions.

ZEGERID with Magnesium Hydroxide is available in two strengths, 40 mg and 20 mg of omeprazole, and is formulated as an immediate-release chewable tablet. Each chewable tablet contains either 40 mg or 20 mg of omeprazole and 600 mg of sodium bicarbonate plus 700 mg of magnesium hydroxide with the following inactive ingredients: hydroxypropyl cellulose, croscarmellose sodium, xylitol, sucralose, flavoring, magnesium stearate, and FD&C Red #40 Aluminum Lake.

CLINICAL PHARMACOLOGY

Omeprazole is acid labile and thus rapidly degraded by gastric acid. ZEGERID with Magnesium Hydroxide is an immediate-release chewable tablet formulation that contains an antacid component (sodium bicarbonate plus magnesium hydroxide) which raises the gastric pH and thus protects omeprazole from acid degradation.

Pharmacokinetics:

Absorption

When ZEGERID with Magnesium Hydroxide chewable tablets are administered on an empty stomach at least 1 hour prior to a meal, the absorption of omeprazole is rapid, with a mean peak plasma level (%CV) of omeprazole being 1763 ng/mL (25%) and time to peak of approximately 30 minutes (range 10-90 min) after a single-dose or repeated-dose administration.

Following single or repeated once daily dosing, peak plasma concentrations of omeprazole from ZEGERID are approximately proportional from 20 to 40 mg doses of omeprazole, but a greater than linear mean AUC (three-fold increase) is observed when doubling the dose to 40 mg. The bioavailability of omeprazole from ZEGERID increases upon repeated administration.

When ZEGERID with Magnesium Hydroxide chewable tablets are administered 1 hour after a meal, the AUC is reduced by approximately 22% relative to administration 1 hour prior to a meal.

Distribution

Omeprazole is bound to plasma proteins. Protein binding is approximately 95%.

Metabolism

Following single dose oral administration of omeprazole, the majority of the dose (about 77%) is eliminated in urine as at least six metabolites. Two metabolites have been identified as hydroxyomeprazole and the corresponding carboxylic acid. The remainder of the dose was recoverable in feces. This implies a significant biliary excretion of the metabolites of omeprazole. Three metabolites have been identified in plasma – the sulfide and sulfone derivatives of omeprazole, and hydroxyomeprazole. These metabolites have very little or no antisecretory activity.

Excretion

Following single dose oral administration of omeprazole, little if any, unchanged drug is excreted in urine. The mean plasma omeprazole half-life in healthy subjects is approximately 1 hour (range 0.4 to 3.1 hours) and the total body clearance is 500-600 mL/min.

Special Populations

Geriatric

The elimination rate of omeprazole was somewhat decreased in the elderly, and bioavailability was increased. Omeprazole was 76% bioavailable when a single 40-mg oral dose of omeprazole (buffered solution) was administered to healthy elderly subjects, versus 58% in young subjects given the same dose. Nearly 70% of the dose was recovered in urine as metabolites of omeprazole and no unchanged drug was detected. The plasma clearance of omeprazole was 250 mL/min (about half that of young subjects) and its plasma half-life averaged one hour, similar to that of young healthy subjects.

Pediatric

The pharmacokinetics of ZEGERID with Magnesium Hydroxide have not been studied in patients < 18 years of age.

Gender

There are no known differences in the absorption or excretion of omeprazole between males and females.

Hepatic Insufficiency

In patients with chronic hepatic disease, the bioavailability of omeprazole from a buffered solution increased to approximately 100% compared to an I.V. dose, reflecting decreased first-pass effect, and the mean plasma half-life of the drug increased to nearly 3 hours compared to the mean half-life of 1 hour in normal subjects. Plasma clearance averaged 70 mL/min, compared to a value of 500-600 mL/min in normal subjects.

Renal Insufficiency

In patients with chronic renal impairment, whose creatinine clearance ranged between 10 and 62 mL/min/1.73 m^2, the disposition of omeprazole from a buffered solution was very similar to that in healthy subjects, although there was a slight increase in bioavailability. Because urinary excretion is a primary route of excretion of omeprazole metabolites, their elimination slowed in proportion to the decreased creatinine clearance.

ZEGERID chewable tablets contain magnesium hydroxide (292 mg of Mg++); therefore, magnesium levels should be closely monitored when using this product in patients with renal failure.

Asians

In pharmacokinetic studies of single 20-mg omeprazole doses, an increase in AUC of approximately four-fold was noted in Asian subjects compared to Caucasians.

Dose adjustment, particularly where maintenance of healing of erosive esophagitis is indicated, for the hepatically impaired and Asian subjects should be considered.

Drug-Drug Interactions

When omeprazole 40 mg was given once daily in combination with clarithromycin 500 mg every 8 hours to healthy adult male subjects, the steady-state plasma concentrations of omeprazole were increased by the concomitant administration of clarithromycin [Cmax, AUC(0-24) and T½ increased 30%, 89%, and 34%, respectively].

Pharmacodynamics:

Mechanism of Action

Omeprazole belongs to a class of antisecretory compounds, the substituted benzimidazoles, that do not exhibit anticholinergic or H2 histamine antagonistic properties, but that suppress gastric acid secretion by specific inhibition of the H+/K+ ATPase enzyme system at the secretory surface of the gastric parietal cell. Because this enzyme system is regarded as the acid (proton) pump within the gastric mucosa, omeprazole has been characterized as a gastric acid-pump inhibitor, in that it blocks the final step of acid production. This effect is dose related and leads to inhibition of both basal and stimulated acid secretion irrespective of the stimulus. Animal studies indicate that after rapid disappearance from plasma, omeprazole can be found within the gastric mucosa for a day or more.

Antisecretory Activity

Results from PK/PD studies of the antisecretory effect of repeated once-daily dosing of 40 mg and 20 mg of ZEGERID with Magnesium Hydroxide chewable tablets in healthy subjects are shown in Table 1 below.

Table 1: Effect of ZEGERID® with Magnesium Hydroxide Chewable Tablets on Intragastric pH on Day 7
 | Omeprazole/Sodium Bicarbonate/Magnesium Hydroxide
Parameter | 40 mg/600 mg/700 mg (n = 35) | 20 mg/600 mg/700 mg (n = 29)
% Decrease from Baseline for Integrated Gastric Acidity (mmol*hr/L) | 73% | 72%
Coefficient of variation | 19% | 28%
% Time Gastric pH > 4 (Hours) | 62% (14.9 h) | 57% (13.8 h)
Coefficient of variation | 30% | 32%
Median pH | 5.1 | 4.8
Coefficient of variation | 24% | 29%
Note: Values are medians. All parameters were measured over a 24-hour period.

The antisecretory effect of omeprazole thus lasts far longer than would be expected from the very short (1 hour) plasma half-life, apparently due to irreversible binding to the parietal H+/K+ ATPase enzyme.

Repeated single daily oral doses of ZEGERID have produced nearly 100% inhibition of 24-hour integrated gastric acidity in some subjects.

Enterochromaffin-like (ECL) Cell Effects

In 24-month carcinogenicity studies in rats, a dose-related significant increase in gastric carcinoid tumors and ECL cell hyperplasia was observed in both male and female animals (see PRECAUTIONS, Carcinogenesis, Mutagenesis, Impairment of Fertility). Carcinoid tumors have also been observed in rats subjected to fundectomy or long-term treatment with other proton pump inhibitors or high doses of H2-receptor antagonists. Human gastric biopsy specimens have been obtained from more than 3000 patients treated with omeprazole in long-term clinical trials. The incidence of ECL cell hyperplasia in these studies increased with time; however, no case of ECL cell carcinoids, dysplasia, or neoplasia has been found in these patients. These studies are of insufficient duration and size to rule out the possible influence of long-term administration of omeprazole on the development of any premalignant or malignant conditions.

Serum Gastrin Effects

In studies involving more than 200 patients, serum gastrin levels increased during the first 1 to 2 weeks of once-daily administration of therapeutic doses of omeprazole in parallel with inhibition of acid secretion. No further increase in serum gastrin occurred with continued treatment. In comparison with histamine H2-receptor antagonists, the median increases produced by 20 mg doses of omeprazole were higher (1.3 to 3.6 fold vs. 1.1 to 1.8 fold increase). Gastrin values returned to pretreatment levels, usually within 1 to 2 weeks after discontinuation of therapy.

Other Effects

Systemic effects of omeprazole in the CNS, cardiovascular, and respiratory systems have not been found to date. Omeprazole, given in oral doses of 30 or 40 mg for 2 to 4 weeks, had no effect on thyroid function, carbohydrate metabolism, or circulating levels of parathyroid hormone, cortisol, estradiol, testosterone, prolactin, cholecystokinin, or secretin.

No effect on gastric emptying of the solid and liquid components of a test meal was demonstrated after a single dose of omeprazole 90 mg. In healthy subjects, a single I.V. dose of omeprazole (0.35 mg/kg) had no effect on intrinsic factor secretion. No systematic dose-dependent effect has been observed on basal or stimulated pepsin output in humans. However, when intragastric pH is maintained at 4.0 or above, basal pepsin output is low, and pepsin activity is decreased.

As do other agents that elevate intragastric pH, omeprazole administered for 14 days in healthy subjects produced a significant increase in the intragastric concentrations of viable bacteria. The pattern of the bacterial species was unchanged from that commonly found in saliva. All changes resolved within three days of stopping treatment.

The course of Barrett's esophagus in 106 patients was evaluated in a U.S. double-blind controlled study of omeprazole 40 mg b.i.d. for 12 months followed by 20 mg b.i.d. for 12 months or ranitidine 300 mg b.i.d. for 24 months. No clinically significant impact on Barrett's mucosa by antisecretory therapy was observed. Although neosquamous epithelium developed during antisecretory therapy, complete elimination of Barrett's mucosa was not achieved. No significant difference was observed between treatment groups in development of dysplasia in Barrett's mucosa and no patient developed esophageal carcinoma during treatment. No significant differences between treatment groups were observed in development of ECL cell hyperplasia, corpus atrophic gastritis, corpus intestinal metaplasia, or colon polyps exceeding 3 mm in diameter (see also CLINICAL PHARMACOLOGY, Enterochromaffin-like (ECL) Cell Effects).

Clinical Studies

Duodenal Ulcer Disease

Active Duodenal Ulcer – In a multicenter, double-blind, placebo controlled study of 147 patients with endoscopically documented duodenal ulcer, the percentage of patients healed (per protocol) at 2 and 4 weeks was significantly higher with omeprazole 20 mg once a day than with placebo (p ≤ 0.01). (See Table 2.)

Table 2: Treatment of Active Duodenal Ulcer; % of Patients Healed
 | Omeprazole 20 mg a.m. (n = 99) | Placebo a.m. (n = 48)
Week 2 | 41* | 13
Week 4 | 75* | 27
* (p ≤ 0.01)

Complete daytime and nighttime pain relief occurred significantly faster (p ≤ 0.01) in patients treated with omeprazole 20 mg than in patients treated with placebo. At the end of the study, significantly more patients who had received omeprazole had complete relief of daytime pain (p ≤ 0.05) and nighttime pain (p ≤ 0.01).

In a multicenter, double-blind study of 293 patients with endoscopically documented duodenal ulcer, the percentage of patients healed (per protocol) at 4 weeks was significantly higher with omeprazole 20 mg once a day than with ranitidine 150 mg b.i.d. (p < 0.01). (See Table 3.)

Table 3: Treatment of Active Duodenal Ulcer; % of Patients Healed
 | Omeprazole 20 mg a.m. (n = 145) | Ranitidine 150 mg b.i.d. (n = 148)
Week 2 | 42 | 34
Week 4 | 82* | 63
* (p < 0.01)

Healing occurred significantly faster in patients treated with omeprazole than in those treated with ranitidine 150 mg b.i.d. (p < 0.01).

In a foreign multinational randomized, double-blind study of 105 patients with endoscopically documented duodenal ulcer, 40 mg and 20 mg of omeprazole were compared to 150 mg b.i.d. of ranitidine at 2, 4 and 8 weeks. At 2 and 4 weeks both doses of omeprazole were statistically superior (per protocol) to ranitidine, but 40 mg was not superior to 20 mg of omeprazole, and at 8 weeks there was no significant difference between any of the active drugs. (See Table 4.)

Table 4: Treatment of Active Duodenal Ulcer; % of Patients Healed
 | Omeprazole 40 mg (n = 36) | Omeprazole 20 mg (n = 34) | Ranitidine 150 mg b.i.d. (n = 35)
Week 2 | 83* | 83* | 53
Week 4 | 100* | 97* | 82
Week 8 | 100 | 100 | 94
*(p ≤ 0.01)

Gastric Ulcer

In a U.S. multicenter, double-blind, study of omeprazole 40 mg once a day, 20 mg once a day, and placebo in 520 patients with endoscopically diagnosed gastric ulcer, the following results were obtained. (See Table 5.)

Table 5: Treatment of Gastric Ulcer; % of Patients Healed (All Patients Treated)
 | Omeprazole 40 mg q.d. (n = 214) | Omeprazole 20 mg q.d. (n = 202) | Placebo (n = 104)
Week 4 | 55.6** | 47.5** | 30.8
Week 8 | 82.7**,+ | 74.8** | 48.1
** (p < 0.01) omeprazole 40 mg or 20 mg versus placebo
+ (p < 0.05) omeprazole 40 mg versus 20 mg

For the stratified groups of patients with ulcer size less than or equal to 1 cm, no difference in healing rates between 40 mg and 20 mg was detected at either 4 or 8 weeks. For patients with ulcer size greater than 1 cm, 40 mg was significantly more effective than 20 mg at 8 weeks.

In a foreign, multinational, double-blind study of 602 patients with endoscopically diagnosed gastric ulcer, omeprazole 40 mg once a day, 20 mg once a day, and ranitidine 150 mg twice a day were evaluated. (See Table 6.)

Table 6: Treatment of Gastric Ulcer; % of Patients Healed (All Patients Treated)
 | Omeprazole 40 mg q.d. (n = 187) | Omeprazole 20 mg q.d. (n = 200) | Ranitidine 150 mg b.i.d. (n = 199)
Week 4 | 78.1**,++ | 63.5 | 56.3
Week 8 | 91.4**,++ | 81.5 | 78.4
**(p < 0.01) Omeprazole 40 mg versus ranitidine
++(p < 0.01) Omeprazole 40 mg versus 20 mg

Gastroesophageal Reflux Disease (GERD)

Symptomatic GERD

A placebo controlled study was conducted in Scandinavia to compare the efficacy of omeprazole 20 mg or 10 mg once daily for up to 4 weeks in the treatment of heartburn and other symptoms in GERD patients without erosive esophagitis. Results are shown in Table 7.

Table 7: % Successful Symptomatic Outcomea
 | Omeprazole 20 mg a.m. | Omeprazole 10 mg a.m. | Placebo a.m.
All patients | 46*,† (n = 205) | 31† (n = 199) | 13 (n = 105)
Patients with confirmed GERD | 56*,† (n = 115) | 36† (n = 109) | 14 (n = 59)
a Defined as complete resolution of heartburn
* (p < 0.005) versus 10 mg
† (p < 0.005) versus placebo

Erosive Esophagitis

In a U.S. multicenter double-blind placebo controlled study of 40 mg or 20 mg of omeprazole in patients with symptoms of GERD and endoscopically diagnosed erosive esophagitis of grade 2 or above, the percentage healing rates (per protocol) were as shown in Table 8.

Table 8: % Patients Healed
 | Omeprazole 40 mg (n = 87) | Omeprazole 20 mg (n = 83) | Placebo (n = 43)
Week 4 | 45* | 39* | 7
Week 8 | 75* | 74* | 14
* (p < 0.01) Omeprazole versus placebo.

In this study, the 40-mg dose was not superior to the 20-mg dose of omeprazole in the percentage healing rate. Other controlled clinical trials have also shown that omeprazole is effective in severe GERD. In comparisons with histamine H2-receptor antagonists in patients with erosive esophagitis, grade 2 or above, omeprazole in a dose of 20 mg was significantly more effective than the active controls. Complete daytime and nighttime heartburn relief occurred significantly faster (p < 0.01) in patients treated with omeprazole than in those taking placebo or histamine H2-receptor antagonists.

In this and five other controlled GERD studies, significantly more patients taking 20 mg omeprazole (84%) reported complete relief of GERD symptoms than patients receiving placebo (12%).

Long Term Maintenance Treatment of Erosive Esophagitis

In a U.S. double-blind, randomized, multicenter, placebo controlled study, two dose regimens of omeprazole were studied in patients with endoscopically confirmed healed esophagitis. Results to determine maintenance of healing of erosive esophagitis are shown in Table 9.

Table 9: Life Table Analysis
 | Omeprazole 20 mg q.d. (n = 138) | Omeprazole 20 mg 3 days per week (n = 137) | Placebo (n = 131)
Percent in endoscopic remission at 6 months | 70* | 34 | 11
* (p < 0.01) Omeprazole 20 mg q.d. versus Omeprazole 20 mg 3 consecutive days per week or placebo.

In an international multicenter double-blind study, omeprazole 20 mg daily and 10 mg daily were compared to ranitidine 150 mg twice daily in patients with endoscopically confirmed healed esophagitis. Table 10 provides the results of this study for maintenance of healing of erosive esophagitis.

Table 10: Life Table Analysis
 | Omeprazole 20 mg q.d. (n = 131) | Omeprazole 10 mg q.d. (n = 133) | Ranitidine 150 mg b.i.d. (n = 128)
Percent in endoscopic remission at 12 months | 77* | 58‡ | 46
* (p = 0.01) Omeprazole 20 mg q.d. versus Omeprazole 10 mg q.d. or Ranitidine.
‡ (p = 0.03) Omeprazole 10 mg q.d. versus Ranitidine.

In patients who initially had grades 3 or 4 erosive esophagitis, for maintenance after healing, 20 mg daily of omeprazole was effective, while 10 mg did not demonstrate effectiveness.

INDICATIONS AND USAGE

Duodenal Ulcer

ZEGERID with Magnesium Hydroxide is indicated for short-term treatment of active duodenal ulcer. Most patients heal within four weeks. Some patients may require an additional four weeks of therapy.

Gastric Ulcer

ZEGERID with Magnesium Hydroxide is indicated for short-term treatment (4-8 weeks) of active benign gastric ulcer. (See CLINICAL PHARMACOLOGY, Clinical Studies, Gastric Ulcer.)

Treatment of Gastroesophageal Reflux Disease (GERD)

Symptomatic GERD

ZEGERID with Magnesium Hydroxide is indicated for the treatment of heartburn and other symptoms associated with GERD.

Erosive Esophagitis

ZEGERID with Magnesium Hydroxide is indicated for the short-term treatment (4-8 weeks) of erosive esophagitis which has been diagnosed by endoscopy. (See CLINICAL PHARMACOLOGY, Clinical Studies.)

The efficacy of ZEGERID with Magnesium Hydroxide used for longer than 8 weeks in these patients has not been established. In the rare instance of a patient not responding to 8 weeks of treatment, it may be helpful to give up to an additional 4 weeks of treatment. If there is recurrence of erosive esophagitis or GERD symptoms (eg, heartburn), additional 4-8 week courses of omeprazole may be considered.

Maintenance of Healing of Erosive Esophagitis

ZEGERID with Magnesium Hydroxide is indicated to maintain healing of erosive esophagitis. Controlled studies do not extend beyond 12 months.

CONTRAINDICATIONS

ZEGERID with Magnesium Hydroxide is contraindicated in patients with known hypersensitivity to any components of the formulation.

PRECAUTIONS

General

Symptomatic response to therapy with omeprazole does not preclude the presence of gastric malignancy.

Atrophic gastritis has been noted occasionally in gastric corpus biopsies from patients treated long-term with omeprazole.

Each 20 mg and 40 mg ZEGERID with Magnesium Hydroxide chewable tablet contains 600 mg (7 mEq) of sodium bicarbonate (equivalent to 164 mg of Na+) and 700 mg (24 mEq) of magnesium hydroxide (equivalent to 292 mg of Mg++).

The sodium content of this product should be taken into consideration when administering to patients on a sodium-restricted diet.

Magnesium hydroxide should be used with caution in neonates, elderly, and in patients with renal impairment or renal disease due to increased risk of developing hypermagnesemia and magnesium toxicity. Magnesium hydroxide should not be used in patients with renal failure unless serum magnesium levels are being closely monitored.

Sodium bicarbonate is contraindicated in patients with metabolic alkalosis and hypocalcemia. Sodium bicarbonate should be used with caution in patients with Bartter's syndrome, hypokalemia, respiratory alkalosis, and problems with acid-base balance. Long-term administration of bicarbonate with calcium or milk can cause milk-alkali syndrome.

Information for Patients

ZEGERID with Magnesium Hydroxide should be taken on an empty stomach at least one hour prior to a meal. ZEGERID with Magnesium Hydroxide chewable tablets are available in 40 mg and 20 mg dosage strengths of omeprazole with 600 mg sodium bicarbonate plus 700 mg magnesium hydroxide per tablet.

Directions for Use: DO NOT SWALLOW WHOLE AND DO NOT SUBSTITUTE FOR OTHER ZEGERID DOSAGE FORMS. Chew the tablet and swallow with water. DO NOT USE OTHER LIQUIDS.

Drug Interactions

Omeprazole can prolong the elimination of diazepam, warfarin and phenytoin, drugs that are metabolized by oxidation in the liver. There have been reports of increased INR and prothrombin time in patients receiving proton pump inhibitors, including omeprazole, and warfarin concomitantly. Increases in INR and prothrombin time may lead to abnormal bleeding and even death. Patients treated with proton pump inhibitors and warfarin may need to be monitored for increases in INR and prothrombin time. Although in normal subjects no interaction with theophylline or propranolol was found, there have been clinical reports of interaction with other drugs metabolized via the cytochrome P-450 system (eg, cyclosporine, disulfiram, benzodiazepines). Patients should be monitored to determine if it is necessary to adjust the dosage of these drugs when taken concomitantly with ZEGERID.

Because of its profound and long-lasting inhibition of gastric acid secretion, it is theoretically possible that omeprazole may interfere with absorption of drugs where gastric pH is an important determinant of their bioavailability (eg, ketoconazole, ampicillin esters, and iron salts). In the clinical efficacy trials antacids were used concomitantly with the administration of omeprazole.

Concomitant administration of omeprazole and atazanavir has been reported to reduce the plasma levels of atazanavir.

Concomitant administration of omeprazole and tacrolimus may increase the serum levels of tacrolimus.

Co-administration of omeprazole and clarithromycin have resulted in increases of plasma levels of omeprazole, clarithromycin, and 14-hydroxy-clarithromycin (see also CLINICAL PHARMACOLOGY, Pharmacokinetics).

Carcinogenesis, Mutagenesis, Impairment of Fertility

In two 24-month carcinogenicity studies in rats, omeprazole at daily doses of 1.7, 3.4, 13.8, 44.0 and 140.8 mg/kg/day (approximately 0.5 to 28.5 times the human dose of 40 mg/day, based on body surface area) produced gastric ECL cell carcinoids in a dose-related manner in both male and female rats; the incidence of this effect was markedly higher in female rats, which had higher blood levels of omeprazole. Gastric carcinoids seldom occur in the untreated rat. In addition, ECL cell hyperplasia was present in all treated groups of both sexes. In one of these studies, female rats were treated with 13.8 mg omeprazole/kg/day (approximately 2.8 times the human dose of 40 mg/day, based on body surface area) for one year, then followed for an additional year without the drug. No carcinoids were seen in these rats. An increased incidence of treatment-related ECL cell hyperplasia was observed at the end of one year (94% treated vs 10% controls). By the second year the difference between treated and control rats was much smaller (46% vs 26%) but still showed more hyperplasia in the treated group. Gastric adenocarcinoma was seen in one rat (2%). No similar tumor was seen in male or female rats treated for two years. For this strain of rat no similar tumor has been noted historically, but a finding involving only one tumor is difficult to interpret. In a 52-week toxicity study in Sprague-Dawley rats, brain astrocytomas were found in a small number of males that received omeprazole at dose levels of 0.4, 2, and 16 mg/kg/day (about 0.1 to 3.3 times the human dose of 40 mg/day, based on body surface area). No astrocytomas were observed in female rats in this study. In a 2-year carcinogenicity study in Sprague-Dawley rats, no astrocytomas were found in males and females at the high dose of 140.8 mg/kg/day (about 28.5 times the human dose of 40 mg/day, based on body surface area). A 78-week mouse carcinogenicity study of omeprazole did not show increased tumor occurrence, but the study was not conclusive. A 26-week p53 (+/-) transgenic mouse carcinogenicity study was not positive. Omeprazole was positive for clastogenic effects in an in vitro human lymphocyte chromosomal aberration assay, in one of two in vivo mouse micronucleus tests, and in an in vivo bone marrow cell chromosomal aberration assay. Omeprazole was negative in the in vitro Ames Test, an in vitro mouse lymphoma cell forward mutation assay and an in vivo rat liver DNA damage assay.

Omeprazole at oral doses up to 138 mg/kg/day (about 28 times the human dose of 40 mg/day, based on body surface area) was found to have no effect on the fertility and general reproductive performance in rats.

Pregnancy

Pregnancy Category C

There are no adequate and well-controlled studies on the use of omeprazole in pregnant women. The vast majority of reported experience with omeprazole during human pregnancy is first trimester exposure and the duration of use is rarely specified, e.g., intermittent vs. chronic. An expert review of published data on experiences with omeprazole use during pregnancy by TERIS – the Teratogen Information System – concluded that therapeutic doses during pregnancy are unlikely to pose a substantial teratogenic risk (the quantity and quality of data were assessed as fair).^1

Three epidemiological studies compared the frequency of congenital abnormalities among infants born to women who used omeprazole during pregnancy to the frequency of abnormalities among infants of women exposed to H2-receptor antagonists or other controls. A population-based prospective cohort epidemiological study from the Swedish Medical Birth Registry, covering approximately 99% of pregnancies, reported on 955 infants (824 exposed during the first trimester with 39 of these exposed beyond first trimester, and 131 exposed after the first trimester) whose mothers used omeprazole during pregnancy.^2 In utero exposure to omeprazole was not associated with increased risk of any malformation (odds ratio 0.82, 95% CI 0.50-1.34), low birth weight or low Apgar score. The number of infants born with ventricular septal defects and the number of stillborn infants was slightly higher in the omeprazole exposed infants than the expected number in the normal population. The author concluded that both effects may be random.

A retrospective cohort study reported on 689 pregnant women exposed to either H2-blockers or omeprazole in the first trimester (134 exposed to omeprazole).^3 The overall malformation rate was 4.4% (95% CI 3.6-5.3) and the malformation rate for first trimester exposure to omeprazole was 3.6% (95% CI 1.5-8.1). The relative risk of malformations associated with first trimester exposure to omeprazole compared with nonexposed women was 0.9 (95% CI 0.3-2.2). The study could effectively rule out a relative risk greater than 2.5 for all malformations. Rates of preterm delivery or growth retardation did not differ between the groups.

A controlled prospective observational study followed 113 women exposed to omeprazole during pregnancy (89% first trimester exposures).^4 The reported rates of major congenital malformations was 4% for the omeprazole group, 2% for controls exposed to nonteratogens, and 2.8% in disease-paired controls (background incidence of major malformations 1-5%). Rates of spontaneous and elective abortions, preterm deliveries, gestational age at delivery, and mean birth weight did not differ between the groups. The sample size in this study has 80% power to detect a 5-fold increase in the rate of major malformation.

Several studies have reported no apparent adverse short term effects on the infant when single dose oral or intravenous omeprazole was administered to over 200 pregnant women as premedication for cesarean section under general anesthesia.

Teratology studies conducted in pregnant rats at doses up to 138 mg/kg/day (about 28 times the human dose of 40 mg/day, based on body surface area) and in pregnant rabbits at doses up to 69 mg/kg/day (about 28 times the human dose of 40 mg/day, based on body surface area) did not disclose any evidence for a teratogenic potential of omeprazole.

In rabbits, omeprazole in a dose range of 6.9 to 69 mg/kg/day (about 2.8 to 28 times the human dose of 40 mg/day, based on body surface area) produced dose-related increases in embryo-lethality, fetal resorptions and pregnancy disruptions. In rats, dose-related embryo/fetal toxicity and postnatal developmental toxicity were observed in offspring resulting from parents treated with omeprazole at 13.8 to 138 mg/kg/day (about 2.8 to 28 times the human dose of 40 mg/day, based on body surface area).

Chronic use of sodium bicarbonate may lead to systemic alkalosis and increased sodium intake can produce edema and weight increase.

Hypermagnesemia has been reported in infants whose mothers were using magnesium-containing antacid products chronically in high doses.

There are no adequate and well-controlled studies in pregnant women. Because animal studies and studies in humans cannot rule out the possibility of harm, omeprazole should be used during pregnancy only if the potential benefit to pregnant women justifies the potential risk to the fetus.

Nursing Mothers

Omeprazole concentrations have been measured in breast milk of a woman following oral administration of 20 mg. The peak concentration of omeprazole in breast milk was less than 7% of the peak serum concentration. The concentration will correspond to 0.004 mg of omeprazole in 200 mL of milk. Because omeprazole is excreted in human milk, because of the potential for serious adverse reactions in nursing infants from omeprazole, and because of the potential for tumorigenicity shown for omeprazole in rat carcinogenicity studies, a decision should be taken to discontinue nursing or to discontinue the drug, taking into account the importance of the drug to the mother. In addition, sodium bicarbonate should be used with caution in nursing mothers.

Pediatric Use

Clinical studies have been conducted evaluating delayed-release omeprazole in pediatric patients. There are no adequate and well-controlled studies in pediatric patients with ZEGERID.

Geriatric Use

Omeprazole was administered to over 2000 elderly individuals (≥ 65 years of age) in clinical trials in the U.S. and Europe. There were no differences in safety and effectiveness between the elderly and younger subjects. Other reported clinical experience has not identified differences in response between the elderly and younger subjects, but greater sensitivity of some older individuals cannot be ruled out.

Pharmacokinetic studies with buffered omeprazole have shown the elimination rate was somewhat decreased in the elderly and bioavailability was increased. The plasma clearance of omeprazole was 250 mL/min (about half that of young subjects). The plasma half-life averaged one hour, about the same as that in nonelderly, healthy subjects taking ZEGERID. However, no dosage adjustment is necessary in the elderly. (See CLINICAL PHARMACOLOGY.)

ADVERSE REACTIONS

Omeprazole was generally well tolerated during domestic and international clinical trials in 3096 patients.

In the U.S. clinical trial population of 465 patients, the adverse experiences summarized in Table 11 were reported to occur in 1% or more of patients on therapy with omeprazole. Numbers in parentheses indicate percentages of the adverse experiences considered by investigators as possibly, probably or definitely related to the drug.

Table 11: Adverse Experiences Occurring in 1% or More of Patients on Omeprazole Therapy
 | Omeprazole (n = 465) | Placebo (n = 64) | Ranitidine (n = 195)
Headache | 6.9 (2.4) | 6.3 | 7.7 (2.6)
Diarrhea | 3.0 (1.9) | 3.1 (1.6) | 2.1 (0.5)
Abdominal Pain | 2.4 (0.4) | 3.1 | 2.1
Nausea | 2.2 (0.9) | 3.1 | 4.1 (0.5)
URI | 1.9 | 1.6 | 2.6
Dizziness | 1.5 (0.6) | 0.0 | 2.6 (1.0)
Vomiting | 1.5 (0.4) | 4.7 | 1.5 (0.5)
Rash | 1.5 (1.1) | 0.0 | 0.0
Constipation | 1.1 (0.9) | 0.0 | 0.0
Cough | 1.1 | 0.0 | 1.5
Asthenia | 1.1 (0.2) | 1.6 (1.6) | 1.5 (1.0)
Back Pain | 1.1 | 0.0 | 0.5

Table 12 summarizes the adverse reactions that occurred in 1% or more of omeprazole-treated patients from international double-blind, and open-label clinical trials in which 2,631 patients and subjects received omeprazole.

Table 12: Incidence of Adverse Experiences ≥ 1%; Causal Relationship not Assessed
 | Omeprazole (n = 2631) | Placebo (n = 120)
Body as a Whole, site unspecified
Abdominal pain | 5.2 | 3.3
Asthenia | 1.3 | 0.8
Digestive System
Constipation | 1.5 | 0.8
Diarrhea | 3.7 | 2.5
Flatulence | 2.7 | 5.8
Nausea | 4.0 | 6.7
Vomiting | 3.2 | 10.0
Acid regurgitation | 1.9 | 3.3
Nervous System/Psychiatric
Headache | 2.9 | 2.5

Additional adverse experiences occurring in < 1% of patients or subjects in domestic and/or international trials conducted with omeprazole, or occurring since the drug was marketed, are shown below within each body system. In many instances, the relationship to omeprazole was unclear.

Body As a Whole

Allergic reactions, including, rarely, anaphylaxis (see also Skin below), fever, pain, fatigue, malaise, abdominal swelling.

Cardiovascular

Chest pain or angina, tachycardia, bradycardia, palpitation, elevated blood pressure, and peripheral edema.

Gastrointestinal

Pancreatitis (some fatal), anorexia, irritable colon, flatulence, fecal discoloration, esophageal candidiasis, mucosal atrophy of the tongue, dry mouth, stomatitis. During treatment with omeprazole, gastric fundic gland polyps have been noted rarely. These polyps are benign and appear to be reversible when treatment is discontinued.

Gastroduodenal carcinoids have been reported in patients with Zollinger-Ellison syndrome on long-term treatment with omeprazole. This finding is believed to be a manifestation of the underlying condition, which is known to be associated with such tumors.

Hepatic

Mild and, rarely, marked elevations of liver function tests [ALT (SGPT), AST (SGOT), γ-glutamyl transpeptidase, alkaline phosphatase, and bilirubin (jaundice)]. In rare instances, overt liver disease has occurred, including hepatocellular, cholestatic, or mixed hepatitis, liver necrosis (some fatal), hepatic failure (some fatal), and hepatic encephalopathy.

Metabolic/Nutritional

Hyponatremia, hypoglycemia, and weight gain.

Musculoskeletal

Muscle cramps, myalgia, muscle weakness, joint pain, and leg pain.

Nervous System/Psychiatric

Psychic disturbances including depression, agitation, aggression, hallucinations, confusion, insomnia, nervousness, tremors, apathy, somnolence, anxiety, dream abnormalities; vertigo; paresthesia; and hemifacial dysesthesia.

Respiratory

Epistaxis, pharyngeal pain.

Skin

Rash and rarely, cases of severe generalized skin reactions including toxic epidermal necrolysis (TEN; some fatal), Stevens-Johnson syndrome, and erythema multiforme (some severe); purpura and/or petechiae (some with rechallenge); skin inflammation, urticaria, angioedema, pruritus, photosensitivity, alopecia, dry skin, and hyperhidrosis.

Special Senses

Tinnitus, taste perversion.

Ocular

Blurred vision, ocular irritation, dry eye syndrome, optic atrophy, anterior ischemic optic neuropathy, optic neuritis and double vision.

Urogenital

Interstitial nephritis (some with positive rechallenge), urinary tract infection, microscopic pyuria, urinary frequency, elevated serum creatinine, proteinuria, hematuria, glycosuria, testicular pain, and gynecomastia.

Hematologic

Rare instances of pancytopenia, agranulocytosis (some fatal), thrombocytopenia, neutropenia, leukopenia, anemia, leucocytosis, and hemolytic anemia have been reported.

The incidence of clinical adverse experiences in patients greater than 65 years of age was similar to that in patients 65 years of age or less.

Additional adverse reactions that could be caused by sodium bicarbonate include metabolic alkalosis, seizures, and tetany.

The use of magnesium hydroxide is associated with diarrhea, abdominal cramping, chalky taste, diuresis, dehydration, nausea, and vomiting.

OVERDOSAGE

Reports have been received of overdosage with omeprazole in humans. Doses ranged up to 2400 mg (120 times the usual recommended clinical dose). Manifestations were variable, but included confusion, drowsiness, blurred vision, tachycardia, nausea, vomiting, diaphoresis, flushing, headache, dry mouth, and other adverse reactions similar to those seen in normal clinical experience. (See ADVERSE REACTIONS.) Symptoms were transient, and no serious clinical outcome has been reported when omeprazole was taken alone. No specific antidote for omeprazole overdosage is known. Omeprazole is extensively protein bound and is, therefore, not readily dialyzable. In the event of overdosage, treatment should be symptomatic and supportive.

As with the management of any overdose, the possibility of multiple drug ingestion should be considered. For current information on treatment of any drug overdose, a certified Regional Poison Control Center should be contacted. Telephone numbers are listed in the Physicians' Desk Reference (PDR) or local telephone book.

Single oral doses of omeprazole at 1350, 1339, and 1200 mg/kg were lethal to mice, rats, and dogs, respectively. Animals given these doses showed sedation, ptosis, tremors, convulsions, and decreased activity, body temperature, and respiratory rate and increased depth of respiration.

In addition, a sodium bicarbonate overdose may cause hypocalcemia, hypokalemia, hypernatremia, and seizures.

Similarly, a magnesium overdose may lead to hypermagnesemia. Hypermagnesemia results in a depressant effect on the central nervous system, causing anorexia and nausea, and neuromuscular system. Magnesium toxicity causes hypotension, muscle weakness, and electrographic changes.

DOSAGE AND ADMINISTRATION

ZEGERID with Magnesium Hydroxide (omeprazole/sodium bicarbonate/magnesium hydroxide) is available as chewable tablets in 20 mg and 40 mg strengths for adult use. Directions for use for each indication are summarized in Table 13.

Because ZEGERID chewable tablets contain magnesium hydroxide, the chewable tablets should not be substituted for other dosage forms (eg, ZEGERID Powder for Oral Suspension or ZEGERID Capsules).

Since both the 20-mg and 40-mg chewable tablets contain the same amount of sodium bicarbonate (600 mg) and magnesium hydroxide (700 mg), two 20-mg chewable tablets are not equivalent to one 40-mg chewable tablet; therefore, two 20-mg chewable tablets should not be substituted for one 40-mg chewable tablet.

ZEGERID with Magnesium Hydroxide should be taken on an empty stomach at least one hour before a meal.

Table 13: Recommended Doses of ZEGERID® with Magnesium Hydroxide by Indication for Adults 18 Years and Older
Indication | Recommended Dose | Frequency
Short-Term Treatment of Active Duodenal Ulcer | 20 mg | Once daily for 4 weeks*,+
Benign Gastric Ulcer | 40 mg | Once daily for 4-8 weeks **,+
Gastroesophageal Reflux Disease (GERD)
Symptomatic GERD (with no esophageal erosions) | 20 mg | Once daily for up to 4 weeks^+
Erosive Esophagitis | 20 mg | Once daily for 4-8 weeks^+
Maintenance of Healing of Erosive Esophagitis | 20 mg | Once daily**
* Most patients heal within 4 weeks. Some patients may require an additional 4 weeks of therapy.
** For additional information, see CLINICAL PHARMACOLOGY, Clinical Studies section
^+ For additional information, see INDICATIONS AND USAGE section

Administration of Chewable Tablets

ZEGERID with Magnesium Hydroxide chewable tablets should be chewed and swallowed with water. DO NOT SWALLOW WHOLE. DO NOT USE OTHER LIQUIDS. DO NOT SUBSTITUTE FOR OTHER ZEGERID DOSAGE FORMS.

HOW SUPPLIED

ZEGERID with Magnesium Hydroxide 20-mg Chewable Tablets: Each pink, 18 mm in diameter, round tablet, inscribed with the number “2031” on one side and the Santarus logo on the other side, contains 20 mg omeprazole and 600 mg sodium bicarbonate plus 700 mg magnesium hydroxide.

NDC 68012-152-30 Bottles of 30 chewable tablets

ZEGERID with Magnesium Hydroxide 40-mg Chewable Tablets: Each pink, 18 mm in diameter, round tablet, inscribed with the number “4031” on one side and the Santarus logo on the other side, contains 40 mg omeprazole and 600 mg sodium bicarbonate plus 700 mg magnesium hydroxide.

NDC 68012-154-30 Bottles of 30 chewable tablets

Storage

Store at 25°C (77°F); excursions permitted to 15 - 30°C (59 - 86°F). [See USP Controlled Room Temperature]. Do not store this product at temperatures above 30°C (86°F).

Rx Only

REFERENCES

1. Friedman JM and Polifka JE. Omeprazole. In: Teratogenic Effects of Drugs. A Resource for Clinicians (TERIS). 2nd ed. Baltimore, MD: The Johns Hopkins University Press 2000; p. 516.
2. Kallen BAJ. Use of omeprazole during pregnancy – no hazard demonstrated in 955 infants exposed during pregnancy. Eur Obstet Gynecol Reprod Biol 2001; 96(1):63-8.
3. Ruigómez A, Rodriguez LUG, Cattaruzzi C, et al. Use of cimetidine, omeprazole, and ranitidine in pregnant women and pregnancy outcomes. Am J Epidemiol 1999; 150:476-81.
4. Lalkin A, Loebstein, Addis A, et al. The safety of omeprazole during pregnancy: a multicenter prospective controlled study. Am J Obstet Gynecol 1998; 179:727-30.

SANTARUS, INC.®

ZEGERID® with Magnesium Hydroxide Chewable Tablets are manufactured for Santarus, Inc., San Diego, CA 92130

by: Patheon Pharmaceuticals, Inc. Cincinnati, OH 45237

For more information call 1-888-778-0887

Revised: March 2006

ZEGERID® is a registered trademark of Santarus, Inc.

© 2006 Santarus, Inc.

SUPPLEMENTAL PATIENT MATERIAL

Information for Patients

ZEGERID with Magnesium Hydroxide should be taken on an empty stomach at least one hour prior to a meal. ZEGERID with Magnesium Hydroxide chewable tablets are available in 40 mg and 20 mg dosage strengths of omeprazole with 600 mg sodium bicarbonate plus 700 mg magnesium hydroxide per tablet.

Directions for Use: DO NOT SWALLOW WHOLE AND DO NOT SUBSTITUTE FOR OTHER ZEGERID DOSAGE FORMS. Chew the tablet and swallow with water. DO NOT USE OTHER LIQUIDS.